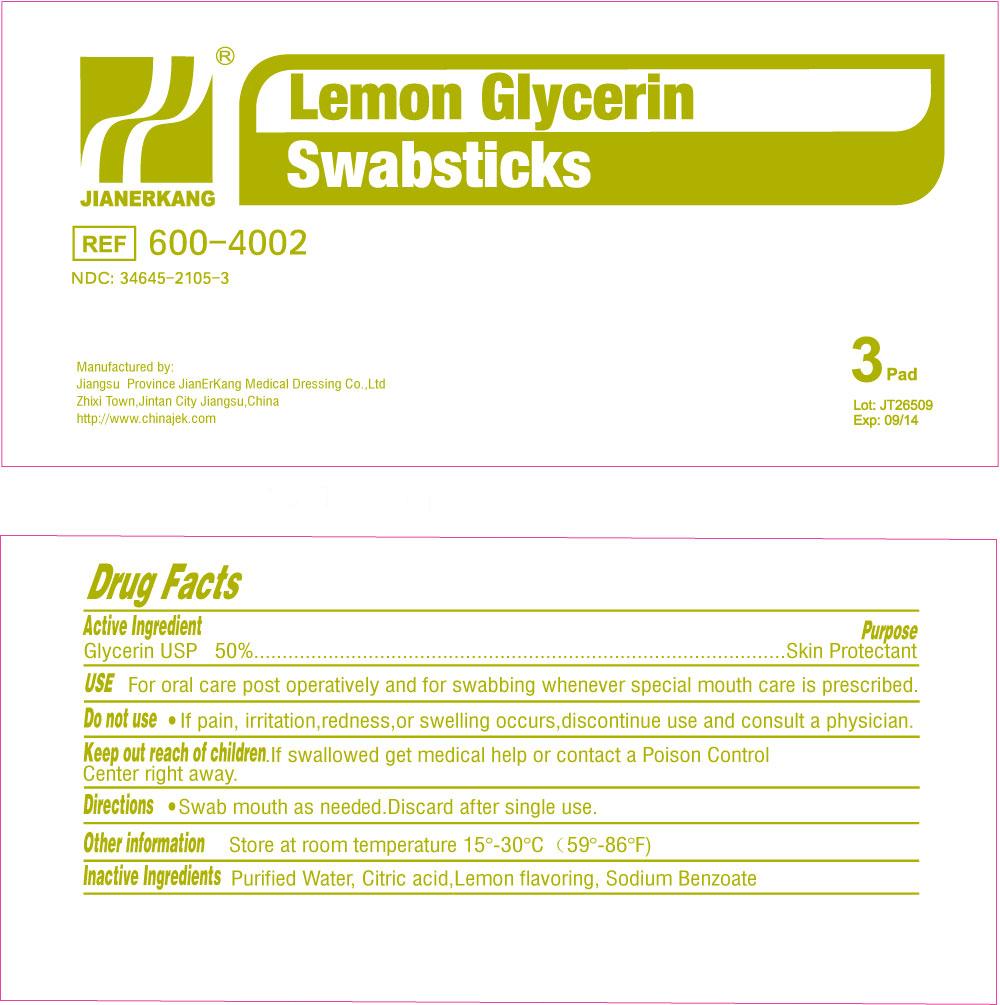 DRUG LABEL: Lemon Glycerin
NDC: 34645-2105 | Form: SWAB
Manufacturer: Jianerkang Medical Co., Ltd
Category: otc | Type: HUMAN OTC DRUG LABEL
Date: 20260116

ACTIVE INGREDIENTS: GLYCERIN 500 mg/1 mL
INACTIVE INGREDIENTS: WATER; CITRIC ACID MONOHYDRATE; SODIUM BENZOATE

Drug Facts

Active Ingredients

Glycerin USP 50%

Purpose

Skin Protectant

Use

For oral care post operatively and for swabbing whenever special mouth care is prescribed

WARNINGS

Do Not Use

If pain, irritation, redness, or swelling occurs, discontinue use and consult a physician.

Keep out reach of children

If swallowed, get medical help or contact Poison Control Center right away

Directions

Swab mouth as needed. Discard after single use.

Other Information

Store at room temperature 15 -30 C (59 -86 F)oooo

Inactive Ingredients

Purified Water, Citric Acid, Lemon Flavoring, Sodium Benzoate